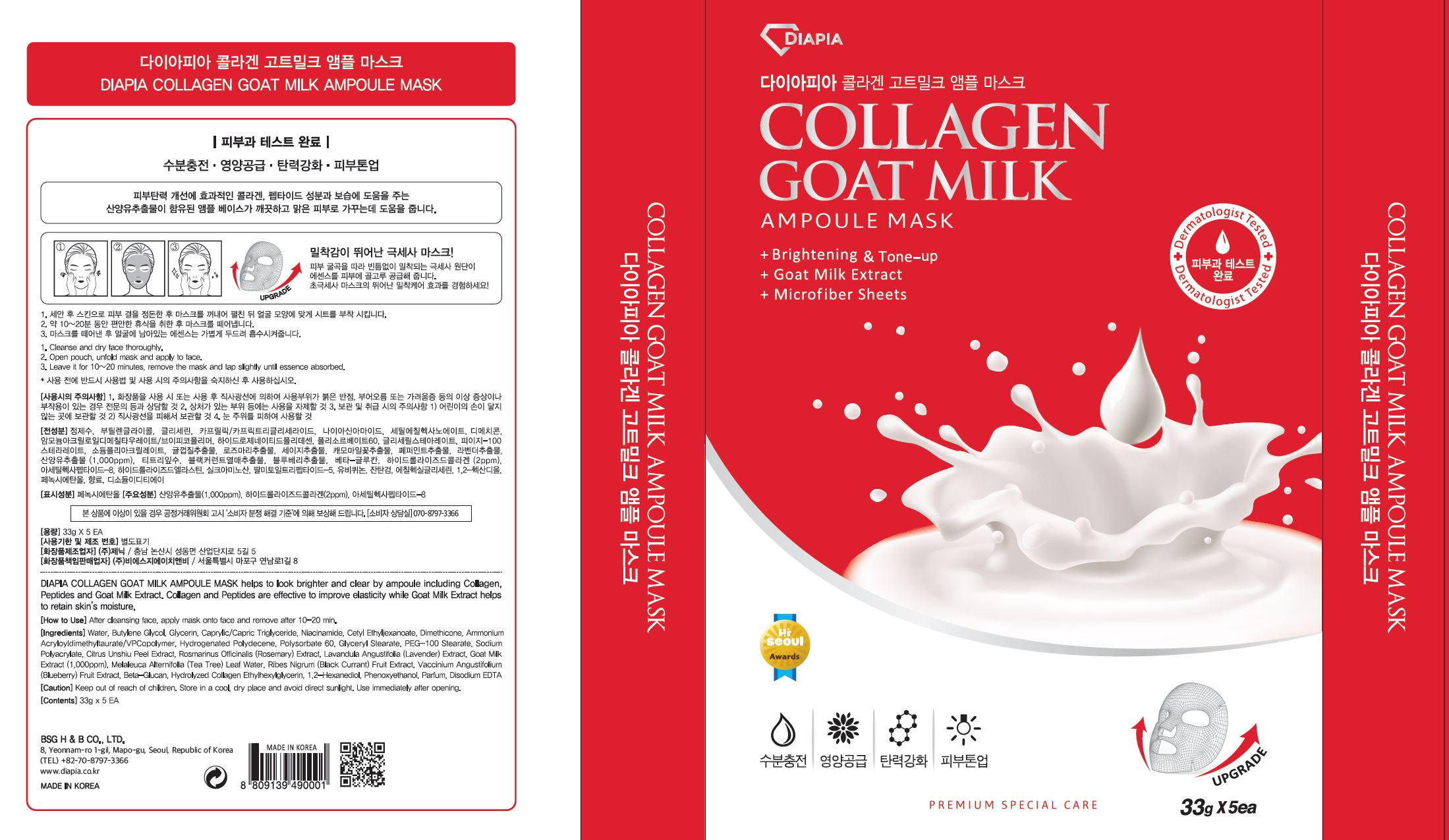 DRUG LABEL: DIAPIA COLLAGEN GOAT MILK AMPOULE MASK
NDC: 71857-0012 | Form: LIQUID
Manufacturer: BSG H & B Co., Ltd.
Category: otc | Type: HUMAN OTC DRUG LABEL
Date: 20211210

ACTIVE INGREDIENTS: NIACINAMIDE 2 g/100 g
INACTIVE INGREDIENTS: WATER

Drug Facts

ACTIVE INGREDIENT

Niacinamide

INACTIVE INGREDIENT

Water, Butylene Glycol, Glycerin, Caprylic/Capric Triglyceride, Dimethicone, Cetyl Ethylhexanoate, 1,2-Hexanediol, Polysorbate 60, Hydrogenetaed Polydecene, Ammonium Acryloyldimethyltaurate/VP Copolymer, Phenoxyethanol, Glyceryl Stearate, PEG-100 Stearate, Goat Milk Extract, Xanthan Gum, Ethylhexylglycerin, Sodium Polyacrylate, Disodium EDTA, Fragrance, Melaleuca Alternifolia (Tea Tree) Leaf Water, Buthylphenyl Methylpropional, Silk Amino Acids, Beta-Glucan, Hydrolyzed Collagen, Hydrolyzed Elastin, Citrus Unshiu Peel Extract, Ribes Nigrum (Black Current) Fruit Extract, Vaccinium Angustifolium (Blueberry) Fruit Extract, Lavandula Angustifolia (Lavender) Extract, Rosmarinus Officinalis (Rosemary) Extract, Salvia Officinalis (Sage) Extract, Chamomilla Recutita (Matricaria) Flower Extract, Mentha Piperita (Peppermint) Extract, Ubiquinone, Palmitoyl Tripeptide-5, Acetyl Hexapeptide-8

PURPOSE

Brightening, Nourishing, Moisturizing, Improving skin elasticity

keep out of reach of the children

INDICATIONS AND USAGE

Cleanse and dry face thoroughly.

Open pouch, unfold mask and apply to face.

Leave it for 10 - 20 minutes, remove the mask and tap slightly until essence

absorbed.

WARNINGS

1.Keep out of reach of children.

2.Store in a cool, dry place and avoid direct sunlight.

3.If abnormal symptoms occur after use, stop use and consult with a skin specialist.

DOSAGE AND ADMINISTRATION

for external use only